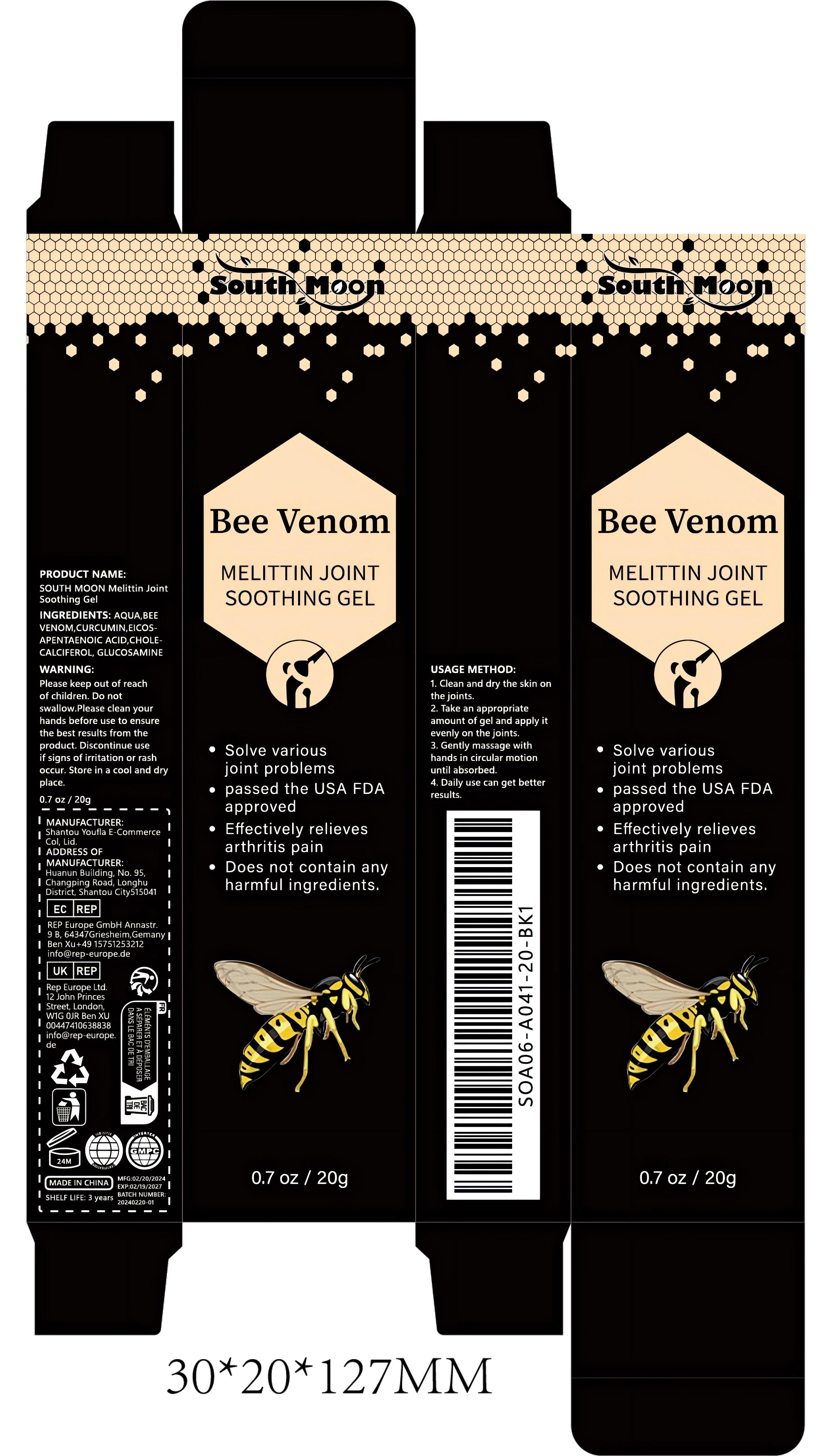 DRUG LABEL: SOUTH MOON Melittin Joint Soothing Gel
NDC: 84732-055 | Form: GEL
Manufacturer: Dongguan Haiyi Technology Co.,Ltd.
Category: otc | Type: HUMAN OTC DRUG LABEL
Date: 20241020

ACTIVE INGREDIENTS: APIS MELLIFERA VENOM 1 mg/20 g; GLUCOSAMINE 1 mg/20 g
INACTIVE INGREDIENTS: WATER; CURCUMIN; CHOLECALCIFEROL; ICOSAPENT

Active ingredient

BEE VENOM

GLUCOSAMINE

Inactive ingredient

AQUA,CURCUMIN,EICOSAPENTAENOIC ACID,CHOLE-CALCIFEROL

Purpose section

1.Solve various joint problems

2.passed the USA FDAapproved

3.Effectively relieves arthritis pain

4.Does not contain anyharmful ingredients.

Warning

Please keep out of reachof children. Do notswallow.Please clean yourhands before use to ensurethe best results from theproduct. Discontinue useif signs of irritation or rashoccur. Store in a cool and dry place.

stop use

This product may cause allergic reactions in asmall number of people.
lf youexperience any discomfort,please stop using it immediately.

not use

Not suitable for use by children, pregnantor breast feeding people.

OUT OF CHILDREN

KEEP THE PRODUCT OUT OF REACH OF CHILDREN to

HOW TO USE

1. Clean and dry the skin onthe joints.

2. Take an appropriateamount of gel and apply itevenly on the joints.

3. Gently massage withhands in circular motionuntil absorbed.

4. Daily use can get betterresults.

Dosage

take an appropriateamount,Use 2-3 times a week